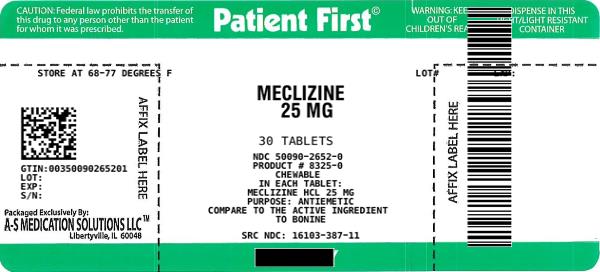 DRUG LABEL: MECLIZINE
NDC: 50090-2652 | Form: TABLET, CHEWABLE
Manufacturer: A-S Medication Solutions
Category: otc | Type: HUMAN OTC DRUG LABEL
Date: 20210901

ACTIVE INGREDIENTS: MECLIZINE HYDROCHLORIDE 25 mg/1 1
INACTIVE INGREDIENTS: CROSCARMELLOSE SODIUM; DEXTROSE, UNSPECIFIED FORM; FD&C RED NO. 40; MAGNESIUM STEARATE; MICROCRYSTALLINE CELLULOSE; SILICON DIOXIDE; SACCHARIN SODIUM; STEARIC ACID

Drug Facts

Active ingredient (in each tablet)

Meclizine HCl 25mg

Purpose

Antiemetic

Uses

prevents and treats nausea, vomiting or dizziness associated with motion sickness

Warnings

Do not use for children under 12 years of age unless directed by a doctor.

Do not take unless directed by a doctor if you have

- glaucoma
- trouble urinating due to an enlarged prostate gland
- a breathing problem such as emphysema or chronic bronchitis

Do not take if you are taking sedatives or tranquilizers, without first consulting your doctor.

When using this product

- do not exceed recommended dosage
- drowsiness may occur
- alcohol, sedatives, and tranquilizers may increase drowsiness
- avoid alcoholic drinks
- be careful when driving a motor vehicle or operating machinery

If pregnant or breast-feeding,

ask a health professional before use.

Keep out of reach of children.

In case of overdose, get medical help or contact a Poison Control Center right away.

Directions

- doage should be taken 1 hour before travel starts

Adults and children 12 years and over | take 1 or 2 tablets once daily or as directed by doctor

Other information

- Tamper Evident: do not use if safety seal under cap is broken or missing
- store at room temperature 20°-25°C (68°-77°F)

Inactive ingredients

Croscarmellose sodium, dextrose, FD&C Red#40, flavor, magnesium stearate, microcrystalline cellulose, silicon dioxide, sodium saccharine, stearic acid

Questions?

Adverse drug event call (866) 562-2756 (M - F, 8AM - 4PM EST).

HOW SUPPLIED

Product: 50090-2652

NDC: 50090-2652-0 30 TABLET, CHEWABLE in a BOTTLE